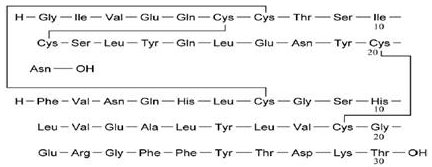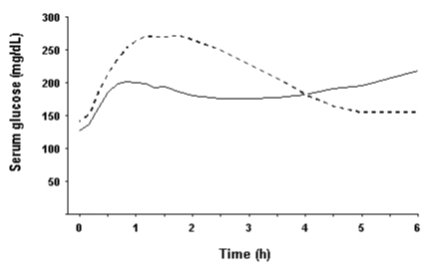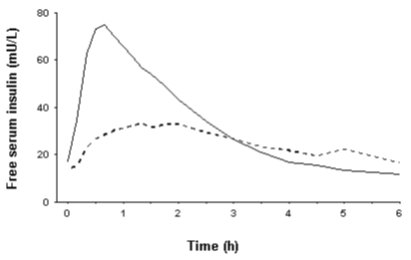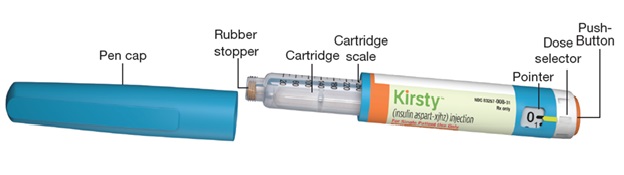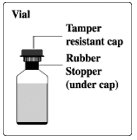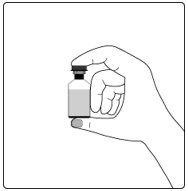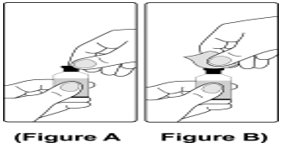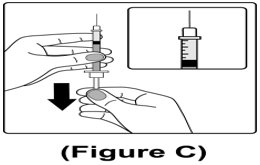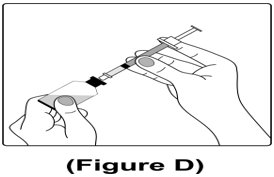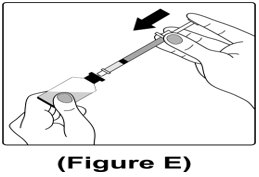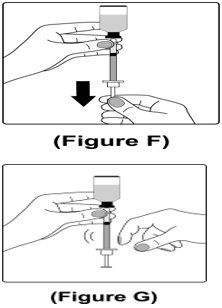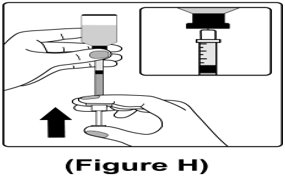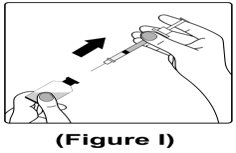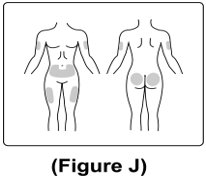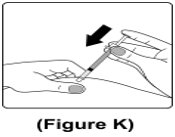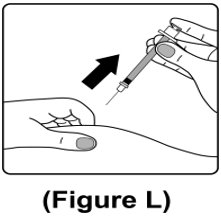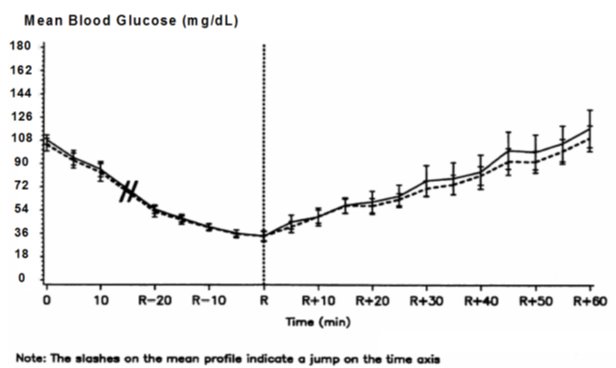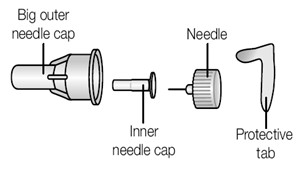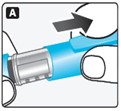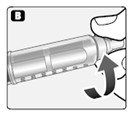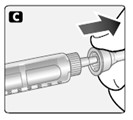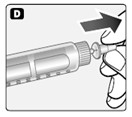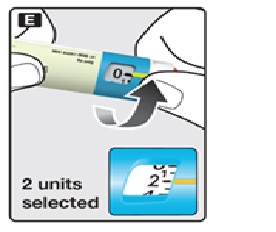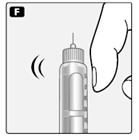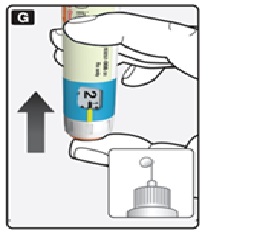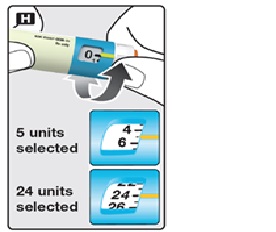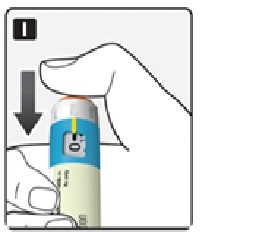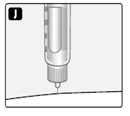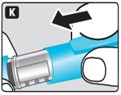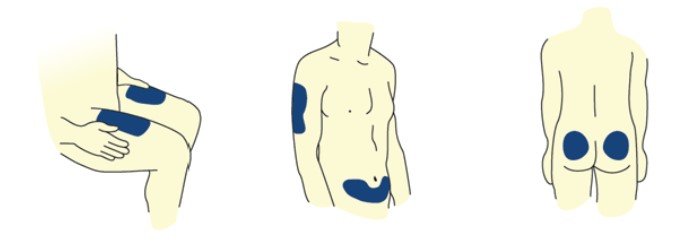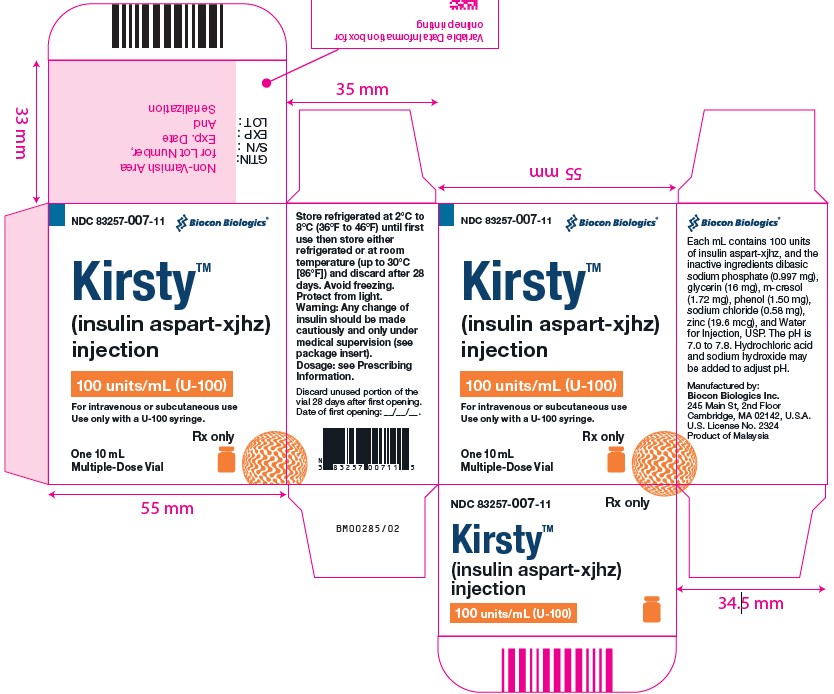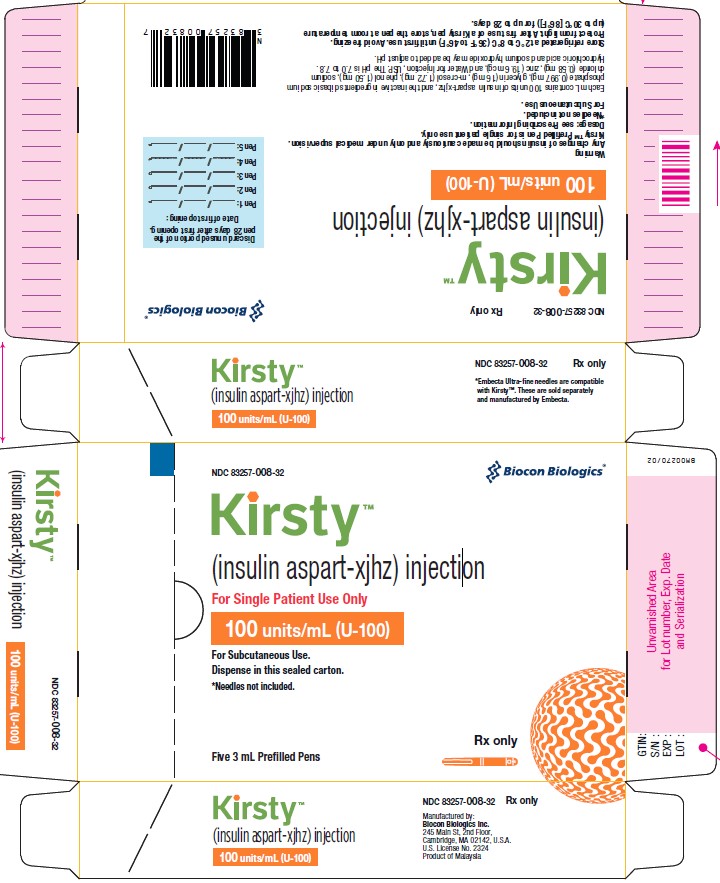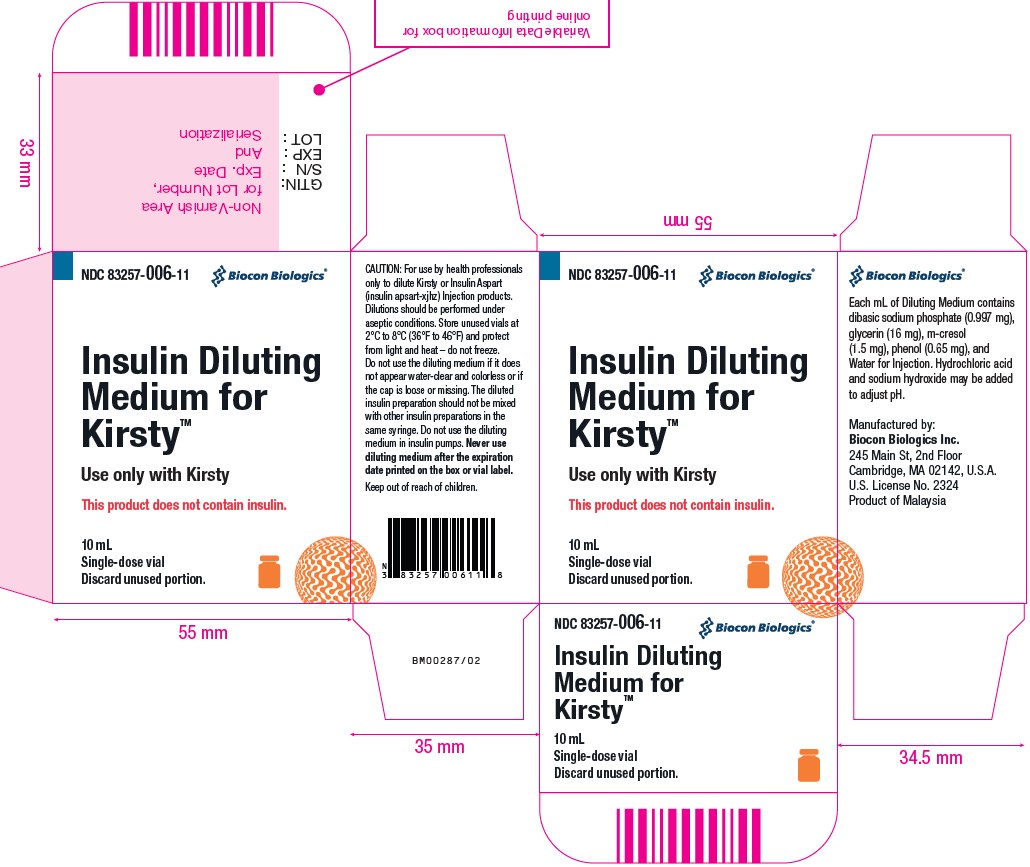 DRUG LABEL: KIRSTY
NDC: 83257-007 | Form: INJECTION, SOLUTION
Manufacturer: Biocon Biologics Inc.
Category: prescription | Type: HUMAN PRESCRIPTION DRUG LABEL
Date: 20250820

ACTIVE INGREDIENTS: INSULIN ASPART 100 [iU]/1 mL
INACTIVE INGREDIENTS: GLYCERIN 16 mg/1 mL; PHENOL 1.5 mg/1 mL; METACRESOL 1.72 mg/1 mL; ZINC 19.6 ug/1 mL; SODIUM PHOSPHATE, DIBASIC, DIHYDRATE 0.997 mg/1 mL; SODIUM CHLORIDE 0.58 mg/1 mL; WATER; HYDROCHLORIC ACID; SODIUM HYDROXIDE

HIGHLIGHTS OF PRESCRIBING INFORMATION

These highlights do not include all the information needed to use KIRSTY safely and effectively. See full prescribing information for KIRSTY.
KIRSTY™ (insulin aspart-xjhz) injection, for subcutaneous or intravenous use
Initial U.S. Approval: 2025
KIRSTY™ (insulin aspart-xjhz) is biosimilar* to NOVOLOG (insulin aspart)

1 INDICATIONS AND USAGE

- KIRSTY is rapid acting human insulin analog indicated to improve glycemic control in adults and pediatric patients with diabetes mellitus (1).

2 DOSAGE AND ADMINISTRATION

- See Full Prescribing Information for important preparation, administration and dosage instructions (2.1, 2.2, 2.3, 2.4, 2.5).
- Subcutaneous injection (2.2):
  - Inject subcutaneously within 5-10 minutes before a meal into the abdominal area, thigh, buttocks or upper arm.
  - Rotate injection sites within the same region from one injection to the next to reduce risk of lipodystrophy and localized cutaneous amyloidosis.
  - Should generally be used in regimens with an intermediate- or long-acting insulin.
- Continuous Subcutaneous Infusion (Insulin Pump) (2.2):
  - Refer to the insulin infusion pump user manual to see if KIRSTY or NOVOLOG can be used with the insulin pump, in which case KIRSTY can be used with the pump. Use in accordance with the insulin pump instructions for use.
  - Administer by continuous subcutaneous infusion using an insulin pump in a region recommended in the instructions from the pump manufacturer.
  - Rotate the injection sites within the same region from one injection to the next to reduce the risk of lipodystrophy and localized cutaneous amyloidosis.
  - Do not mix with other insulins or diluents in the pump.
- Intravenous Administration (2.2):
  - Dilute KIRSTY to concentrations from 0.05 unit/mL to 1 unit/mL insulin aspart-xjhz in infusion systems using polypropylene infusion bags.
  - KIRSTY is stable in infusion fluids such as 0.9% Sodium Chloride Injection, USP.
- Individualize and adjust the dosage of KIRSTY based on route of administration, the individual's metabolic needs, blood glucose monitoring results and glycemic control goal (2.4).
- Dosage adjustments may be needed with changes in physical activity, changes in meal patterns (i.e., macronutrient content or timing of food intake), changes in renal or hepatic function or during acute illness (2.4).

3 DOSAGE FORMS AND STRENGTHS

Injection: 100 units/mL (U-100) of insulin aspart-xjhz available as:

- 3 mL single-patient-use prefilled pen (3)
- 10 mL multiple-dose vial (3)

4 CONTRAINDICATIONS

- During episodes of hypoglycemia (4).
- Hypersensitivity to insulin aspart products or any of the excipients in KIRSTY.

5 WARNINGS AND PRECAUTIONS

- Never share a KIRSTY prefilled pen, needles or syringes between patients, even if the needle is changed (5.1).
- Hyperglycemia or hypoglycemia with changes in insulin regimen: Make changes to a patient’s insulin regimen (e.g., insulin strength, manufacturer, type, injection site or method of administration) under close medical supervision with increased frequency of blood glucose monitoring (5.2).
- Hypoglycemia: May be life-threatening. Increase frequency of glucose monitoring with changes to: insulin dosage, concomitantly administered glucose lowering medications, meal pattern, physical activity; and in patients with renal or hepatic impairments and hypoglycemia unawareness (5.3).
- Medication Errors: Accidental mix-ups between insulin products can occur. Instruct patients to check insulin labels before injection (5.4).
- Hypersensitivity reactions: Severe, life-threatening, generalized allergy, including anaphylaxis, may occur. Discontinue KIRSTY, treat, and monitor if indicated (5.5).
- Hypokalemia: May be life-threatening. Monitor potassium levels in patients at risk of hypokalemia and treat if indicated (5.6).
- Fluid retention and heart failure with concomitant use of thiazolidinediones (TZDs): Observe for signs and symptoms of heart failure; consider dosage reduction or discontinuation if heart failure occurs (5.7).
- Hyperglycemia and Ketoacidosis Due to Insulin Pump Device Malfunction: Monitor glucose and administer KIRSTY by subcutaneous injection if pump malfunction occurs (5.8).

6 ADVERSE REACTIONS

Adverse reactions observed with insulin aspart products include hypoglycemia, allergic reactions, local injection site reactions, lipodystrophy, rash, and pruritus (6).

To report SUSPECTED ADVERSE REACTIONS, contact Biocon Biologics at 1-833-986-1468 or FDA at 1-800-FDA-1088 or www.fda.gov/medwatch.

7 DRUG INTERACTIONS

- Drugs that may increase the risk of hypoglycemia: antidiabetic agents, ACE inhibitors, angiotensin II receptor blocking agents, disopyramide, fibrates, fluoxetine, monoamine oxidase inhibitors, pentoxifylline, pramlintide, salicylates, somatostatin analog (e.g., octreotide), and sulfonamide antibiotics (7).
- Drugs that may decrease the blood glucose lowering effect: atypical antipsychotics, corticosteroids, danazol, diuretics, estrogens, glucagon, isoniazid, niacin, oral contraceptives, phenothiazines, progestogens (e.g., in oral contraceptives), protease inhibitors, somatropin, sympathomimetic agents (e.g., albuterol, epinephrine, terbutaline), and thyroid hormones (7).
- Drugs that may increase or decrease the blood glucose lowering effect: alcohol, beta-blockers, clonidine, lithium salts, and pentamidine (7).
- Drugs that may blunt the signs and symptoms of hypoglycemia: beta-blockers, clonidine, guanethidine, and reserpine (7).

* Biosimilar means that the biological product is approved based on data demonstrating that it is highly similar to an FDA-approved biological product, known as a reference product, and that there are no clinically meaningful differences between the biosimilar product and the reference product. Biosimilarity of KIRSTY has been demonstrated for the condition(s) of use (e.g., indication(s), dosing regimen(s)), strength(s), dosage form(s), and route(s) of administration described in its Full Prescribing Information.

FULL PRESCRIBING INFORMATION

1 INDICATIONS AND USAGE

KIRSTY is indicated to improve glycemic control in adults and pediatric patients with diabetes mellitus.

2 DOSAGE AND ADMINISTRATION

2.1 Important Preparation and Administration Instructions

- Always check insulin labels before administration [see Warnings and Precautions (5.4)].
- Inspect KIRSTY visually before use. It should appear clear and colorless. Do not use KIRSTY if particulate matter or coloration is seen.
- In patients with visual impairment who rely on audible clicks to dial their dose, use KIRSTY prefilled pen with caution.
- Do not mix KIRSTY with other insulins when administering using a continuous subcutaneous infusion pump.

2.2 Preparation and Administration Instructions for the Approved Routes of Administration

Subcutaneous Injection

- Inject KIRSTY subcutaneously within 5-10 minutes before a meal into the abdominal area, thigh, buttocks or upper arm.
- Rotate injection sites within the same region from one injection to the next to reduce the risk of lipodystrophy and localized cutaneous amyloidosis. Do not inject into areas of lipodystrophy or localized cutaneous amyloidosis [see Warnings and Precautions (5.2) and Adverse Reactions (6.1, 6.3)].
- Dial the KIRSTY prefilled pen in 1-unit increments.
- Generally use KIRSTY (administered by subcutaneous injection) in regimens with an intermediate-or long-acting insulin.
- May dilute KIRSTY with Insulin Diluting Medium for KIRSTY for subcutaneous injection. Diluting one part KIRSTY to:
  • Nine parts diluent will yield a concentration one-tenth that of KIRSTY (equivalent to U-10).
  • One part diluent will yield a concentration one-half that of KIRSTY (equivalent to U-50). Discard any unused diluent after opening the vial of Insulin Diluting Medium for KIRSTY.

Continuous Subcutaneous Infusion (Insulin Pump)

- Can use this KIRSTY product with the continuous subcutaneous insulin infusion pumps labeled for use with KIRSTY or NOVOLOG. Refer to the insulin pump user manual to see if KIRSTY or NOVOLOG can be used with the insulin pump, in which case KIRSTY can be used with the pump. Use KIRSTY in accordance with the insulin pump system’s instructions for use.
- Train patients using continuous subcutaneous insulin fusion pump therapy to administer insulin by injection and have alternate insulin therapy available in case of pump failure.
- Administer KIRSTY by continuous subcutaneous infusion in a region recommended in the instructions from the pump manufacturer. Rotate infusion sites within the same region to reduce the risk of lipodystrophy or localized cutaneous amyloidosis [see Warnings and Precautions (5.2) and Adverse Reactions (6.1, 6.3)].
- Instruct patients to follow healthcare provider recommendations when setting basal and meal time infusion rate.

- Change the KIRSTY in the reservoir at least every 7 days or according to the pump user manual, whichever is shorter. Follow the KIRSTY-specific information for in-use time because KIRSTY-specific information may differ from general pump manual instructions.
- Change the infusion set and the infusion set insertion site according to the manufacturer’s user manual.
- Do not dilute or mix KIRSTY when administering by continuous subcutaneous infusion.
- Do not expose KIRSTY in the pump reservoir to temperatures greater than 98.6°F (37°C).

Intravenous Administration

- Administer KIRSTY intravenously only under medical supervision with close monitoring of blood glucose and potassium levels to avoid hypoglycemia and hypokalemia [see Warnings and Precautions (5.3, 5.6) and How Supplied/Storage and Handling (16.2)].
- Dilute KIRSTY to concentrations from 0.05 unit/mL to 1 unit/mL insulin aspart-xjhz in infusion systems using polypropylene infusion bags. KIRSTY is stable in infusion fluids such as 0.9% Sodium Chloride Injection, USP.

2.3 Dosage Recommendations

- Individualize the dosage of KIRSTY based on the route of administration, the patient's metabolic needs, blood glucose monitoring results and glycemic control goal.
- Dosage adjustments may be needed with changes in physical activity, changes in meal patterns (i.e., macronutrient content or timing of food intake), changes in renal or hepatic function or during acute illness [see Warnings and Precautions (5.2, 5.3) and Use in Specific Populations (8.6, 8.7)].
- When switching from another insulin to KIRSTY, a different dosage of KIRSTY may be needed [see Warnings and Precautions (5.2)].
- During changes to a patient’s insulin regimen, increase the frequency of blood glucose monitoring [see Warnings and Precautions (5.2)].

2.4 Dosage Modifications for Drug Interactions

Dosage modification may be needed when KIRSTY is used concomitantly with certain drugs [see Drug Interactions (7)].

2.5 Instructions for Mixing KIRSTY with Other Insulins

The table below includes instructions regarding mixing KIRSTY with other insulins.
Subcutaneous; injection route | • KIRSTY may only be mixed with NPH insulin preparations.; • If KIRSTY is mixed with NPH insulin, withdraw KIRSTY into the syringe first and inject immediately after mixing.
Continuous; subcutaneous infusion; route (Insulin Pump) | Do not mix KIRSTY with any other insulin.

3 DOSAGE FORMS AND STRENGTHS

Injection: 100 units/mL (U-100) is a clear and colorless solution available as:

- 10 mL multiple-dose vial
- 3 mL single-patient-use prefilled pen

4 CONTRAINDICATIONS

KIRSTY is contraindicated

- During episodes of hypoglycemia [see Warnings and Precautions (5.3)]
- In patients with hypersensitivity to insulin aspart products or any of the excipients in KIRSTY [see Warnings and Precautions (5.5)]

5 WARNINGS AND PRECAUTIONS

5.1 Never Share a KIRSTY Prefilled Pen, Needles or Syringes Between Patients

KIRSTY prefilled pens should never be shared between patients, even if the needle is changed. Patients using KIRSTY vials must never share needles or syringes with another person. Sharing poses a risk for transmission of blood-borne pathogens.

5.2 Hyperglycemia or Hypoglycemia with Changes in Insulin Regimen

Changes in an insulin regimen (e.g., insulin strength, manufacturer, type, injection site or method of administration) may affect glycemic control and predispose to hypoglycemia [see Warnings and Precautions (5.3)] or hyperglycemia. Repeated insulin injections into areas of lipodystrophy or localized cutaneous amyloidosis have been reported to result in hyperglycemia; and a sudden change in the injection site (to an unaffected area) has been reported to result in hypoglycemia [see Adverse Reactions (6.1, 6.3)].

Make any changes to a patient’s insulin regimen under close medical supervision with increased frequency of blood glucose monitoring. Advise patients who have repeatedly injected into areas of lipodystrophy or localized cutaneous amyloidosis to change the injection site to unaffected areas and closely monitor for hypoglycemia. For patients with type 2 diabetes, dosage adjustments of concomitant anti-diabetic products may be needed.

5.3 Hypoglycemia

Hypoglycemia is the most common adverse reaction of all insulins, including insulin aspart products. Severe hypoglycemia can cause seizures, may lead to unconsciousness, may be life threatening or cause death. Hypoglycemia can impair concentration ability and reaction time; this may place an individual and others at risk in situations where these abilities are important (e.g., driving or operating other machinery).

Hypoglycemia can happen suddenly and symptoms may differ in each individual and change over time in the same individual. Symptomatic awareness of hypoglycemia may be less pronounced in patients with longstanding diabetes in patients with diabetic nerve disease, in patients using medications that block the sympathetic nervous system (e.g., beta-blockers) [see Drug Interactions (7)], or in patients who experience recurrent hypoglycemia.

Risk Factors for Hypoglycemia

The risk of hypoglycemia after an injection is related to the duration of action of the insulin and, in general, is highest when the glucose lowering effect of the insulin is maximal. As with all insulins, the glucose lowering effect time course of insulin aspart products may vary in different individuals or at different times in the same individual and depends on many conditions, including the area of injection as well as the injection site blood supply and temperature [see Clinical Pharmacology (12.2)]. Other factors which may increase the risk of hypoglycemia include changes in meal pattern (e.g., macronutrient content or timing of meals), changes in level of physical activity, or changes to concomitantly administered medication [see Drug Interactions (7)]. Patients with renal or hepatic impairment may be at higher risk of hypoglycemia [see Use in Specific Populations (8.6, 8.7)].

Risk Mitigation Strategies for Hypoglycemia

Patients and caregivers must be educated to recognize and manage hypoglycemia. Self-monitoring of blood glucose plays an essential role in the prevention and management of hypoglycemia; increased frequency of blood glucose monitoring is recommended. In patients at higher risk for hypoglycemia and patients who have reduced symptomatic awareness of hypoglycemia; increased frequency of blood glucose monitoring is recommended.

5.4 Hypoglycemia Due to Medication Errors

Accidental mix-ups between insulin products have been reported. To avoid medication errors between KIRSTY and other insulins, instruct patients to always check the insulin label before each injection.

5.5 Hypersensitivity Reactions

Severe, life-threatening, generalized allergy, including anaphylaxis, can occur with insulins, including insulin aspart products. If hypersensitivity reactions occur, discontinue KIRSTY; treat per standard of care and monitor until symptoms and signs resolve [see Adverse Reactions (6)]. KIRSTY is contraindicated in patients who have had hypersensitivity reactions to insulin aspart products or any of the excipients in KIRSTY [see Contraindications (4)].

5.6 Hypokalemia

All insulins, including insulin aspart products, can cause a shift in potassium from the extracellular to intracellular space, possibly leading to hypokalemia. Untreated hypokalemia may cause respiratory paralysis, ventricular arrhythmia, and death. Monitor potassium levels in patients at risk for hypokalemia if indicated (e.g., patients using potassium-lowering medications, patients taking medications sensitive to serum potassium concentration).

5.7 Fluid Retention and Heart Failure with Concomitant Use of PPAR-gamma Agonists

Thiazolidinediones (TZDs), which are peroxisome proliferator-activated receptor (PPAR)-gamma agonists, can cause dose-related fluid retention, particularly when used in combination with insulin. Fluid retention may lead to or exacerbate heart failure. Patients treated with insulin, including KIRSTY, and a PPAR-gamma agonist should be observed for signs and symptoms of heart failure. If heart failure develops, it should be managed according to current standards of care, and discontinuation or dose reduction of the PPAR-gamma agonist must be considered.

5.8 Hyperglycemia and Ketoacidosis Due to Insulin Pump Device Malfunction

Malfunction of the insulin pump or insulin infusion set or insulin degradation can rapidly lead to hyperglycemia and ketoacidosis. Prompt identification and correction of the cause of hyperglycemia or ketosis is necessary. Interim subcutaneous injections with KIRSTY may be required. Patients using continuous subcutaneous insulin infusion pump therapy must be trained to administer insulin by injection and have alternate insulin therapy available in case of pump failure [see How Supplied/Storage and Handling (16.2) and Patient Counseling Information (17)].

6 ADVERSE REACTIONS

The following adverse reactions are also discussed elsewhere:

- Hypoglycemia [see Warnings and Precautions (5.3)]
- Hypoglycemia Due to Medication Errors [see Warnings and Precautions (5.4)]
- Hypersensitivity Reactions [see Warnings and Precautions (5.5)]
- Hypokalemia [see Warnings and Precautions (5.6)]

6.1 Clinical Trials Experience

Because clinical trials are conducted under widely varying designs, the adverse reaction rates reported in one clinical trial may not be easily compared to those rates reported in another clinical trial, and may not reflect the rates actually observed in clinical practice. The safety of insulin aspart was evaluated in two treat-to-target trials of 6 months duration, conducted in patients with type 1 diabetes or type 2 diabetes [see Clinical Studies (14)].

The data in Table 1 reflect the exposure of 596 patients with type 1 diabetes to insulin aspart in one clinical trial with a mean exposure duration to insulin aspart of 24 weeks. The mean age was 39 years. Fifty-one percent were male, 94% were Caucasian, 2% were Black and 4% were other races. The mean body mass index (BMI) was 25.6 kg/m^2. The mean duration of diabetes was 15.7 years and the mean HbA1c at baseline was 7.9%.

The data in Table 2 reflect the exposure of 91 patients with type 2 diabetes to insulin aspart in one clinical trial with a mean exposure duration to insulin aspart of 24 weeks. The mean age was 57 years. Sixty-three percent were male, 76% were Caucasian, 9% were Black and 15% were other races. The mean BMI was 29.7 kg/m^2. The mean duration of diabetes was 12.7 years and the mean HbA1c at baseline was 8.1%.

Common adverse reactions were defined as events that occurred in ≥5%, excluding hypoglycemia, of the population studied. Common adverse events that occurred at the same rate or greater for insulin aspart-treated patients than in comparator-treated patients during clinical trials in patients with type 1 diabetes mellitus and type 2 diabetes mellitus (other than hypoglycemia) are listed in Table 1 and Table 2, respectively.

Table 1: Adverse reactions that occurred in ≥ 5% of Type 1 Diabetes Mellitus Adult Patients treated with insulin aspart and at the same rate or greater on insulin aspart than on comparator
 | Insulin Aspart + NPH (%); (n= 596) | Regular Human Insulin + NPH (%); (n= 286)
Headache | 12 | 10
Injury accidental | 11 | 10
Nausea | 7 | 5
Diarrhea | 5 | 3

Table 2: Adverse reactions that occurred in ≥ 5% of Type 2 Diabetes Mellitus Adult Patients treated with insulin aspart and at the same rate or greater on insulin aspart than on comparator
 | Insulin Aspart + NPH (%); (n= 91) | Human Regular Insulin + NPH (%); (n= 91)
Hyporeflexia | 11 | 7
Onychomycosis | 10 | 5
Sensory disturbance | 9 | 7
Urinary tract infection | 8 | 7
Chest pain | 5 | 3
Headache | 5 | 3
Skin disorder | 5 | 2
Abdominal pain | 5 | 1
Sinusitis | 5 | 1

Severe Hypoglycemia

Hypoglycemia is the most commonly observed adverse reaction in patients using insulin, including insulin aspart products. The rates of reported hypoglycemia depend on the definition of hypoglycemia used, diabetes type, insulin dose, intensity of glucose control, background therapies, and other intrinsic and extrinsic patient factors. For these reasons, comparing rates of hypoglycemia in clinical trials for insulin aspart with the incidence of hypoglycemia for other products may be misleading and also, may not be representative of hypoglycemia rates that will occur in clinical practice.

Severe hypoglycemia was defined as hypoglycemia associated with central nervous system symptoms and requiring the intervention of another person or hospitalization. The incidence of severe hypoglycemia in:

- Adult and pediatric patients with type 1 diabetes mellitus who received subcutaneous insulin aspart was 17% at 24 weeks and 6% at 24 weeks, respectively [see Clinical Studies (14)].

- Adult patients with type 2 diabetes mellitus who received subcutaneous insulin aspart was 10% at 24 weeks.

- Adult and pediatric patients with type 1 diabetes mellitus, who received insulin aspart via continuous subcutaneous insulin infusion by external pump was 2% at 16 weeks and 10% at 16 weeks respectively.

No severe hypoglycemic episodes were reported in adult patients with type 2 diabetes mellitus receiving insulin aspart via continuous subcutaneous insulin infusion by external pump at 16 weeks.

Allergic Reactions

Some patients taking insulin, including insulin aspart products have experienced erythema, local edema, and pruritus at the site of injection. These conditions were usually self-limiting. Severe cases of generalized allergy (anaphylaxis) have been reported.

Adverse Reactions Associated with Insulin Initiation and Glucose Control Intensification

Intensification or rapid improvement in glucose control has been associated with a transitory, reversible ophthalmologic refraction disorder, worsening of diabetic retinopathy, and acute painful peripheral neuropathy. However, long-term glycemic control decreases the risk of diabetic retinopathy and neuropathy.

Lipodystrophy

Administration of insulin, including insulin aspart products, subcutaneously and via subcutaneous insulin infusion by external pump, has resulted in lipoatrophy (depression in the skin) or lipohypertrophy (enlargement or thickening of tissue) in some patients [see Dosage and Administration (2.2)].

Peripheral Edema

Insulins, including insulin aspart products, may cause sodium retention and edema, particularly if previously poor metabolic control is improved by intensified insulin therapy.

Weight Gain

Weight gain has occurred with insulins, including insulin aspart products, and has been attributed to the anabolic effects of insulin and the decrease in glucosuria.

6.2 Immunogenicity

As with all therapeutic proteins, there is potential for immunogenicity. The detection of antibody formation is highly dependent on the sensitivity and specificity of the assay. Additionally, the observed incidence of antibody (including neutralizing antibody) positivity in an assay may be influenced by several factors including assay methodology, sample handling, timing of sample collection, concomitant medications, and underlying disease. For these reasons, comparison of the incidence of antibodies in the studies described below with the incidence of antibodies in other studies or to other insulin aspart products may be misleading.

In a 6-month study with a 6-month extension in adult subjects with type 1 diabetes, 99.8% of patients who received insulin aspart were positive for anti-insulin antibodies (AIA) at least once during the study, including 97.2% that were positive at baseline. A total of 92.1% of patients who received insulin aspart were positive for anti-drug antibodies (ADA) at least once during the study, including 64.6% that were positive at baseline.

In a phase 3 type 1 diabetes clinical trial of insulin aspart, initial increase in titers of antibodies to insulin, followed by a decrease to baseline values, was observed in regular human insulin and insulin aspart treatment groups with similar incidences. These antibodies did not cause deterioration in glycemic control or necessitate increases in insulin dose.

6.3 Post Marketing Experience

The following adverse reactions have been identified during post-approval use of insulin aspart products. Because these adverse reactions are reported voluntarily from a population of uncertain size, it is generally not possible to reliably estimate their frequency or establish a causal relationship to drug exposure.

Medication errors have been reported in which other insulins have been accidentally substituted for insulin aspart products.

Localized cutaneous amyloidosis at the injection site has occurred with insulin aspart products. Hyperglycemia has been reported with repeated insulin injections into areas of localized cutaneous amyloidosis; hypoglycemia has been reported with a sudden change to an unaffected injection site.

7 DRUG INTERACTIONS

The table below presents clinically significant drug interactions with KIRSTY

Drugs That May Increase the Risk of Hypoglycemia
Drugs: | Antidiabetic agents, ACE inhibitors, angiotensin II receptor blocking agents, disopyramide, fibrates, fluoxetine, monoamine oxidase inhibitors, pentoxifylline, pramlintide, salicylates, somatostatin analog (e.g., octreotide), and sulfonamide antibiotics.
Intervention: | Dose adjustment and increased frequency of glucose monitoring may be required when KIRSTY is concomitantly administered with these drugs.
Drugs That May Decrease the Blood Glucose Lowering Effect of KIRSTY
Drugs: | Atypical antipsychotics (e.g., olanzapine and clozapine), corticosteroids, danazol, diuretics, estrogens, glucagon, isoniazid, niacin, oral contraceptives, phenothiazines, progestogens (e.g., in oral contraceptives), protease inhibitors, somatropin, sympathomimetic agents (e.g., albuterol, epinephrine, terbutaline), and thyroid hormones.
Intervention: | Dose adjustment and increased frequency of glucose monitoring may be required when KIRSTY is concomitantly administered with these drugs.
Drugs That May Increase or Decrease the Blood Glucose Lowering Effect of KIRSTY
Drugs: | Alcohol, beta-blockers, clonidine, and lithium salts. Pentamidine may cause hypoglycemia, which may sometimes be followed by hyperglycemia.
Intervention: | Dose adjustment and increased frequency of glucose monitoring may be required when KIRSTY is concomitantly administered with these drugs.
Drugs That May Blunt Signs and Symptoms of Hypoglycemia
Drugs: | Beta-blockers, clonidine, guanethidine, and reserpine
Intervention: | Increased frequency of glucose monitoring may be required when KIRSTY is concomitantly administered with these drugs.

8 USE IN SPECIFIC POPULATIONS

8.1 Pregnancy

Risk Summary

Available information from published randomized controlled trials with insulin aspart products use during the second trimester of pregnancy have not reported an association with insulin aspart products and major birth defects or adverse maternal or fetal outcomes (see Data). There are risks to the mother and fetus associated with poorly controlled diabetes in pregnancy (see Clinical Considerations).

In animal reproduction studies, administration of subcutaneous insulin aspart to pregnant rats and rabbits during the period of organogenesis did not cause adverse developmental effects at exposures 8-times and equal to the human subcutaneous dose of 1 unit/kg/day, respectively.

Pre- and post-implantation losses and visceral/skeletal abnormalities were seen at higher exposures, which are considered secondary to maternal hypoglycemia. These effects were similar to those observed in rats administered regular human insulin (see Data).

In the U.S. general population, the estimated background risk of major birth defects and miscarriage in clinically recognized pregnancies is 2 to 4% and 15 to 20%, respectively. The estimated background risk of major birth defects is 6 to 10% in women with pre-gestational diabetes with a periconceptual HbA1c >7% and has been reported to be as high as 20 to 25% in women with a periconceptual HbA1c >10%. The estimated background risk of miscarriage for the indicated population is unknown.

Clinical Considerations

Disease-Associated Maternal and/or Embryo-Fetal Risk

Poorly controlled diabetes in pregnancy increases the maternal risk for diabetic ketoacidosis, preeclampsia, spontaneous abortions, preterm delivery, and delivery complications. Poorly controlled diabetes increases the fetal risk for major birth defects, stillbirth, and macrosomia related morbidity.

Data

Human Data

Published data from 5 randomized controlled trials of 441 pregnant women with diabetes mellitus treated with insulin aspart products during the late 2nd trimester of pregnancy did not identify an association of insulin aspart products with major birth defects or adverse maternal or fetal outcomes. However, these studies cannot definitely establish the absence of any risk because of methodological limitations, including a variable duration of treatment and small size of the majority of the trials.

Animal Data

Fertility, embryo-fetal and pre- and postnatal development studies have been performed with insulin aspart and regular human insulin in rats and rabbits. In a combined fertility and embryo-fetal development study in rats, insulin aspart was administered before mating, during mating, and throughout pregnancy. Further, in a pre- and postnatal development study insulin aspart was given throughout pregnancy and during lactation to rats. In an embryo-fetal development study insulin aspart was given to female rabbits during organogenesis. The effects of insulin aspart did not differ from those observed with subcutaneous regular human insulin. Insulin aspart, like human insulin, caused pre- and post-implantation losses and visceral/skeletal abnormalities in rats at a dose of 200 units/kg/day (approximately 32 times the human subcutaneous dose of 1 unit/kg/day, based on human exposure equivalents) and in rabbits at a dose of 10 units/kg/day (approximately three times the human subcutaneous dose of 1 unit/kg/day, based on human exposure equivalents). No significant effects were observed in rats at a dose of 50 units/kg/day and in rabbits at a dose of 3 units/kg/day. These doses are approximately 8 times the human subcutaneous dose of 1 unit/kg/day for rats and equal to the human subcutaneous dose of 1 unit/kg/day for rabbits, based on human exposure equivalents. The effects are considered secondary to maternal hypoglycemia.

8.2 Lactation

Risk Summary

There are no data on the presence of insulin aspart products in human milk, the effects on the breastfed infant, or the effect on milk production. One small published study reported that exogenous insulin, including insulin aspart, was present in human milk. However, there is insufficient information to determine the effects of insulin aspart products on the breastfed infant. The developmental and health benefits of breastfeeding should be considered along with the mother’s clinical need for KIRSTY, and any potential adverse effects on the breastfed infant from KIRSTY, or from the underlying maternal condition.

8.4 Pediatric Use

The safety and effectiveness of KIRSTY to improve glycemic control have been established in pediatric patients with diabetes mellitus. Use of KIRSTY for this indication is supported by evidence from an adequate and well-controlled study of insulin aspart in 283 pediatric patients with type 1 diabetes mellitus aged 6 to 18 years and from studies in adults with diabetes mellitus [see Adverse Reactions (6.1), Clinical Pharmacology (12.3), and Clinical Studies (14.1)].

8.5 Geriatric Use

Of the total number of patients (n=1,375) treated with insulin aspart in 3 controlled clinical studies, 2.6% (n=36) were 65 years of age or over. One-half of these patients had type 1 diabetes (18/1285) and the other half had type 2 diabetes (18/90). The HbA1c response to insulin aspart, as compared to regular human insulin, did not differ by age.

8.6 Renal Impairment

Patients with renal impairment may be at increased risk of hypoglycemia and may require more frequent KIRSTY dose adjustment and more frequent blood glucose monitoring [see Warnings and Precautions (5.3) and Clinical Pharmacology (12.3)].

8.7 Hepatic Impairment

Patients with hepatic impairment may be at increased risk of hypoglycemia and may require more frequent KIRSTY dose adjustment and more frequent blood glucose monitoring [see Warnings and Precautions (5.3) and Clinical Pharmacology (12.3)].

10 OVERDOSAGE

Excess insulin administration may cause hypoglycemia and hypokalemia [see Warnings and Precautions (5.3, 5.6)]. Mild episodes of hypoglycemia usually can be treated with oral glucose. Adjustments in drug dosage, meal patterns, or exercise may be needed. More severe episodes with coma, seizure, or neurologic impairment may be treated with intramuscular/subcutaneous glucagon or concentrated intravenous glucose. Sustained carbohydrate intake and observation may be necessary because hypoglycemia may recur after apparent clinical recovery. Hypokalemia must be corrected appropriately.

11 DESCRIPTION

Insulin aspart-xjhz is a rapid-acting human insulin analog homologous with regular human insulin with the exception of a single substitution of the amino acid proline by aspartic acid in position B28 and is produced by recombinant DNA technology utilizing Pichia pastoris. Insulin aspart-xjhz has the empirical formula C256H381N65O79S6 and a molecular weight of 5825.8 Da.

Figure 1. Structural formula of insulin aspart-xjhz.

KIRSTY (insulin aspart-xjhz) injection is a sterile, clear, and colorless solution for subcutaneous or intravenous use. Each mL contains 100 units of insulin aspart-xjhz, and the inactive ingredients dibasic sodium phosphate (0.997 mg), glycerin (16 mg), m-cresol (1.72 mg), phenol (1.50 mg), sodium chloride (0.58 mg), zinc (19.6 mcg), and Water for Injection, USP. KIRSTY has a pH of 7.0-7.8. Hydrochloric acid 1% and/or sodium hydroxide 1% may be added to adjust pH.

12 CLINICAL PHARMACOLOGY

12.1 Mechanism of Action

The primary activity of insulin, including insulin aspart products, is the regulation of glucose metabolism. Insulin and its analogs lower blood glucose by stimulating peripheral glucose uptake, especially by skeletal muscle and fat, and by inhibiting hepatic glucose production. Insulin inhibits lipolysis and proteolysis, and enhances protein synthesis.

12.2 Pharmacodynamics

Pharmacodynamics of insulin aspart After Subcutaneous Administration

The pharmacodynamic profile of insulin aspart given subcutaneously in 22 patients with type 1 diabetes is shown in Figure 2. The maximum glucose-lowering effect of insulin aspart occurred between 1 and 3 hours after subcutaneous injection (0.15 units/kg). The duration of action for insulin aspart is 3 to 5 hours. The time course of action of insulin and insulin analogs such as insulin aspart products may vary considerably in different individuals or within the same individual. The parameters of insulin aspart activity (time of onset, peak time and duration) as designated in Figure 2 should be considered only as general guidelines. The rate of insulin absorption and onset of activity is affected by the site of injection, exercise, and other variables [see Warnings and Precautions (5.3)].

Figure 2. Serial mean serum glucose collected up to 6 hours following a single 0.15 units/kg pre-meal dose of insulin aspart (solid curve) or regular human insulin (hatched curve) injected immediately before a meal in 22 patients with type 1 diabetes.

Pharmacodynamics of insulin aspart After Intravenous Administration

A double-blind, randomized, two-way crossover study in 16 patients with type 1 diabetes demonstrated that intravenous infusion of insulin aspart resulted in a blood glucose profile that was similar to that after intravenous infusion with regular human insulin. Insulin aspart or human insulin was infused until the patient’s blood glucose decreased to 36 mg/dL, or until the patient demonstrated signs of hypoglycemia (rise in heart rate and onset of sweating), defined as the time of autonomic reaction (R) (see Figure 3).

Figure 3. Mean blood glucose profiles following intravenous infusion of insulin aspart (hatched curve) and regular human insulin (solid curve) in 16 patients with type 1 diabetes. R represents the time of autonomic reaction.

12.3 Pharmacokinetics

Absorption and Bioavailability

In studies in healthy volunteers (total n=107) and patients with type 1 diabetes (total n=40), the median time to maximum concentration of insulin aspart in these trials was 40 to 50 minutes versus 80 to 120 minutes, for regular human insulin respectively.

The relative bioavailability of insulin aspart (0.15 units/kg) compared to regular human insulin indicates that the two insulins are absorbed to a similar extent.

In a clinical trial in patients with type 1 diabetes, insulin aspart and regular human insulin, both administered subcutaneously at a dose of 0.15 units/kg body weight, reached mean maximum concentrations of 82 and 36 mU/L, respectively.

Distribution

Insulin aspart has a low binding affinity to plasma proteins (<10%), similar to that seen with regular human insulin.

Figure 4. Serial mean serum free insulin concentration collected up to 6 hours following a single 0.15 units/kg pre-meal dose of insulin aspart (solid curve) or regular human insulin (hatched curve) injected immediately before a meal in 22 patients with type 1 diabetes.

Metabolism and Elimination

In a randomized, double-blind, crossover study 17 healthy Caucasian male subjects between 18 and 40 years of age received an intravenous infusion of either insulin aspart or regular human insulin at 1.5 mU/kg/min for 120 minutes. The mean insulin clearance was similar for the two groups with mean values of 1.2 L/h/kg for the insulin aspart group and 1.2 L/h/kg for the regular human insulin group.

After subcutaneous administration in normal male volunteers (n=24), insulin aspart was eliminated with an average apparent half-life of 81 minutes.

Specific Populations

Pediatric Patients

The pharmacokinetic and pharmacodynamic properties of insulin aspart and regular human insulin were evaluated in a single dose study in 18 pediatric patients with type 1 diabetes in 2 age groups: 6-12 years, n=9 and 13-17 years (Tanner grade ≥ 2), n=9. The relative differences in pharmacokinetics and pharmacodynamics in the pediatric patients with type 1 diabetes in both age groups between insulin aspart and regular human insulin were similar to those in healthy adult subjects and adults with type 1 diabetes.

Geriatric Patients

The pharmacokinetic and pharmacodynamic properties of insulin aspart and regular human insulin were investigated in a single dose study in 18 subjects with type 2 diabetes who were ≥ 65 years of age. The relative differences in pharmacokinetics and pharmacodynamics in geriatric patients with type 2 diabetes between insulin aspart and regular human insulin were similar to those in younger adults.

Male and Female Patients

In healthy volunteers given a single subcutaneous dose of insulin aspart 0.06 units/kg, no difference in insulin aspart levels was seen between males and females based on comparison of AUC (0-10h) or Cmax.

Obese Patients

A single subcutaneous dose of 0.1 units/kg insulin aspart was administered in a study of 23 patients with type 1 diabetes and a wide range of body mass index (BMI, 22-39 kg/m^2). The pharmacokinetic parameters, AUC and Cmax, of insulin aspart were generally unaffected by BMI in the different groups – BMI 19-23 kg/m^2 (n=4); BMI 23-27 kg/m^2 (n=7); BMI 27-32 kg/m^2 (n=6) and BMI >32 kg/m^2 (n=6). Clearance of insulin aspart was reduced by 28% in patients with BMI >32 kg/m^2 compared to patients with BMI <23 kg/m^2.

Patients with Renal Impairment

A single subcutaneous dose of 0.08 units/kg insulin aspart was administered in a study to subjects with either normal renal function (n=6) creatinine clearance (CLcr) (> 80 mL/min) or mild (n=7; CLcr = 50-80 mL/min), moderate (n=3; CLcr = 30-50 mL/min) or severe (but not requiring hemodialysis) (n=2; CLcr = <30 mL/min) renal impairment. In this study, there was no apparent effect of creatinine clearance values on AUC and Cmax of insulin aspart.

Patients with Hepatic Impairment

A single subcutaneous dose of 0.06 units/kg insulin aspart was administered in an open-label, single-dose study of 24 subjects (n=6/group) with different degree of hepatic impairment (mild, moderate and severe) having Child-Pugh Scores ranging from 0 (healthy volunteers) to 12 (severe hepatic impairment). In this study, there was no correlation between the degree of hepatic impairment and any insulin aspart pharmacokinetic parameter.

13 NONCLINICAL TOXICOLOGY

13.1 Carcinogenesis, Mutagenesis, Impairment of Fertility

Standard 2-year carcinogenicity studies in animals have not been performed to evaluate the carcinogenic potential of insulin aspart products. In 52-week studies, Sprague-Dawley rats were dosed subcutaneously with insulin aspart at 10, 50, and 200 units/kg/day (approximately 2, 8, and 32 times the human subcutaneous dose of 1.0 units/kg/day, based on units/body surface area, respectively). At a dose of 200 units/kg/day, insulin aspart increased the incidence of mammary gland tumors in females when compared to untreated controls. The relevance of these findings to humans is unknown.

Insulin aspart was not genotoxic in the following tests: Ames test, mouse lymphoma cell forward gene mutation test, human peripheral blood lymphocyte chromosome aberration test, in vivo micronucleus test in mice, and in ex vivo UDS test in rat liver hepatocytes.

In fertility studies in male and female rats, at subcutaneous doses up to 200 units/kg/day (approximately 32 times the human subcutaneous dose, based on units/body surface area), no direct adverse effects on male and female fertility, or general reproductive performance of animals was observed.

13.2 Animal Toxicology and/or Pharmacology

In standard biological assays in mice and rabbits, one unit of insulin aspart has the same glucose-lowering effect as one unit of regular human insulin.

14 CLINICAL STUDIES

14.1 Overview of Clinical Studies

The safety and effectiveness of subcutaneous insulin aspart were compared to regular human insulin in 596 type 1 diabetes adult, 187 pediatric type 1 diabetes, and 91 adult type 2 diabetes patients using NPH as basal insulin (see Tables 3, 4, 5). The reduction in glycated hemoglobin (HbA1c) was similar to regular human insulin.

The safety and effectiveness of insulin aspart administered by continuous subcutaneous insulin infusion (CSII) by external pump were compared to buffered regular human insulin (administered by CSII), to lispro (administered by CSII) and compared to insulin aspart injections and NPH injection. Overall, the reduction in HbA1c was similar to the comparator.

14.2 Clinical Studies in Adult and Pediatric Patients with Type 1 Diabetes with Subcutaneous Injections

Type 1 Diabetes - Adults (see Table 3)

Two 24-week, open-label, active-controlled studies were conducted to compare the safety and efficacy of insulin aspart to regular human insulin injection in adult patients with type 1 diabetes. Because the two study designs and results were similar, data are shown for only one study (see Table 3).

The mean age of the trial population was 39 years and mean duration of diabetes was 15.7 years. Fifty-one percent were male. Ninety-four percent were Caucasian, 2% were Black and 4% were Other. The mean BMI was approximately 25.6 kg/m^2.

Insulin aspart was administered by subcutaneous injection immediately prior to meals and regular human insulin was administered by subcutaneous injection 30 minutes before meals. NPH insulin was administered as the basal insulin in either single or divided daily doses. Changes in HbA1c were comparable for the two treatment regimens in this study (Table 3).

Table 3. Type 1 Diabetes Mellitus – Adult (insulin aspart plus NPH insulin vs. regular human insulin plus NPH insulin)
 | Insulin Aspart + NPH; (n=596) | Regular Human; Insulin + NPH; (n=286)
Baseline HbA1c (%) [Values are Mean ± SD] | 7.9 ±1.1 | 8.0 ± 1.2
Change from Baseline HbA1c (%) | -0.1 ± 0.8 | 0.0 ± 0.8
Treatment Difference in HbA1c, Mean (95% confidence interval) | -0.2 (-0.3, -0.1)

Type 1 Diabetes – Pediatric (see Table 4)

The efficacy of insulin aspart to improve glycemic control in pediatric patients with type 1 diabetes mellitus is based on an adequate and well-controlled trial of regular human insulin in pediatric patients with type 1 diabetes mellitus (Table 4). This 24-week, parallel-group study of pediatric patients with type 1 diabetes (n = 283), aged 6 to 18 years, compared two subcutaneous multiple-dose treatment regimens: insulin aspart (n=187) or regular human insulin (n=96). NPH insulin was administered as the basal insulin. Similar effects on HbA1c were observed in both treatment groups (Table 4).

Subcutaneous administration of insulin aspart and regular human insulin have also been compared in pediatric patients with type 1 diabetes (n=26) aged 2 to 6 years with similar effects on HbA1c.

Table 4. Pediatric Subcutaneous Administration of insulin aspart in Type 1 Diabetes (24 weeks; n=283)
 | Insulin Aspart + NPH; (n=187) | Regular Human; Insulin + NPH; (n=96)
Baseline HbA1c (%) [Values are Mean ± SD] | 8.3 ± 1.2 | 8.3 ± 1.3
Change from Baseline HbA1c (%) | 0.1± 1.0 | 0.1± 1.1
Treatment Difference in HbA1c, Mean (95% confidence interval) | -0.2 (-0.5, 0.1)

14.3 Clinical Studies in Adults with Type 2 Diabetes with Subcutaneous Injections

Type 2 Diabetes - Adults (see Table 5)

One six-month, open-label, active-controlled study was conducted to compare the safety and efficacy of insulin aspart to regular human insulin in patients with type 2 diabetes (Table 5).

The mean age of the trial population was 56.6 years and mean duration of diabetes was 12.7 years. Sixty-three percent were male. Seventy-six percent were Caucasian, 9% were Black and 15% were Other. The mean BMI was approximately 29.7 kg/m^2.

Insulin aspart was administered by subcutaneous injection immediately prior to meals and regular human insulin was administered by subcutaneous injection 30 minutes before meals. NPH insulin was administered as the basal insulin in either single or divided daily doses. Changes in HbA1c were comparable for the two treatment regimens.

Table 5. Subcutaneous insulin aspart Administration in Type 2 Diabetes (6 months; n=176)
 | Insulin Aspart + NPH; (n=90) | Regular Human; Insulin + NPH; (n=86)
Baseline HbA1c (%) [Values are Mean ± SD] | 8.1 ± 1.2 | 7.8 ± 1.1
Change from Baseline HbA1c (%) | -0.3 ± 1.0 | -0.1 ± 0.8
Treatment Difference in HbA1c, Mean (95% confidence interval) | - 0.1 (-0.4, 0.1)

14.4 Clinical Studies in Adults and Pediatrics with Type 1 Diabetes Using Continuous Subcutaneous Insulin Infusion (CSII) by External Pump

Type 1 Diabetes – Adult (see Table 6)

Two open-label, parallel design studies (6 weeks [n=29] and 16 weeks [n=118]) compared insulin aspart to buffered regular human insulin (Velosulin) in adults with type 1 diabetes receiving a subcutaneous infusion with an external insulin pump.

The mean age of the trial population was 42.3 years. Thirty-nine percent were male. Ninety-eight percent were Caucasian and 2% were Black.

The two treatment regimens had comparable changes in HbA1c.

Table 6. Adult Insulin Pump Study in Type 1 Diabetes (16 weeks; n=118)
 | Insulin Aspart; (n=59) | Buffered human; insulin; (n=59)
Baseline HbA1c (%) [Values are Mean ± SD] | 7.3 ± 0.7 | 7.5 ± 0.8
Change from Baseline HbA1c (%) | 0.0 ± 0.5 | 0.2 ± 0.6
Treatment Difference in HbA1c, Mean (95% confidence interval) | 0.2 (-0.1, 0.4)

Type 1 Diabetes – Pediatric (see Table 7)

A randomized, 16-week, open-label, parallel design study of pediatric patients with type 1 diabetes (n=298) aged 4-18 years compared two subcutaneous infusion regimens administered via an external insulin pump: insulin aspart (n=198) or insulin lispro (n=100). These two treatments resulted in comparable changes from baseline in HbA1c (see Table 7).

Table 7. Pediatric Insulin Pump Study in Type 1 Diabetes (16 weeks; n=298)
 | Insulin Aspart; (n=198) | Lispro; (n=100)
Baseline HbA1c (%) [Values are Mean ± SD] | 8.0 ± 0.9 | 8.2 ± 0.8
Change from Baseline HbA1c (%) | -0.1 ± 0.8 | -0.1 ± 0.7
Treatment Difference in HbA1c, Mean (95% confidence interval) | -0.1 (-0.3, 0.1)

14.5 Clinical Studies in Adults with Type 2 Diabetes Using Continuous Subcutaneous Insulin Infusion (CSII) by External Pump

Type 2 Diabetes – Adults (see Table 8)

An open-label, 16-week parallel design trial compared pre-prandial insulin aspart injection in conjunction with NPH injections to insulin aspart administered by continuous subcutaneous infusion in 127 adults with type 2 diabetes.

The mean age of the trial population was 55.1 years. Sixty-four percent were male. Eighty percent were Caucasian, 12% were Black and 8% were Other. The mean BMI was approximately 32.2 kg/m^2.

The two treatment groups had similar reductions in HbA1c (Table 8).

Table 8. Pump Therapy in Type 2 Diabetes (16 weeks; n=127)
 | Insulin Aspart pump; (n=66) | Insulin Aspart + NPH; (n=61)
Baseline HbA1c (%) [Values are Mean ± SD] | 8.2 ± 1.4 | 8.0 ± 1.1
Change from Baseline HbA1c (%) | -0.6 ± 1.1 | -0.5 ± 0.9
Treatment Difference in HbA1c, Mean (95% confidence interval) | 0.1 (-0.3, 0.4)

16 HOW SUPPLIED/STORAGE AND HANDLING

16.1 How Supplied

KIRSTY (insulin aspart-xjhz) injection 100 units/mL (U-100) is available as a clear and colorless solution in:

One 10 mL multiple-dose vial per carton | 83257-007-11
Five 3 mL single-patient-use prefilled pens per carton | 83257-008-32

The KIRSTY prefilled pen dials in 1-unit increments.

16.2 Recommended Storage

Dispense in the original sealed carton with the enclosed Instructions for Use. Store unused KIRSTY in a refrigerator between 2°C to 8°C (36°F to 46°F). Do not freeze KIRSTY and do not use KIRSTY if it has been frozen. Do not expose KIRSTY to excessive heat or light. Do not withdraw KIRSTY into a syringe and store for later use.

Always remove and discard the needle after each injection from the KIRSTY prefilled pen and store without a needle attached.

The storage conditions are summarized in the following table:

Table 9. Storage conditions for vial and KIRSTY prefilled pen

KIRSTY; presentation | Not in-use (unopened); Room Temperature; (up to 30°C [86°F]) | Not in-use; (unopened); Refrigerated; (2°C to 8°C [36°F to 46°F]) | In-use (opened); Room Temperature; (up to 30°C [86°F])
10 mL multiple-dose vial | 28 days | Until expiration date | 28* days; (refrigerated/room temperature)
3 mL single-; patient-use; prefilled pen | 28 days | Until expiration date | 28 days; (Do not refrigerate)

*For insulin pump use, the total in-use time is 19 days, including 7 days pump in-use time.

Storage in External Insulin Pump:

Change the KIRSTY in the pump reservoir at least every 7 days or according to the pump user manual instructions for KIRSTY or NOVOLOG, whichever is shorter, or after exposure to temperatures that exceed 37°C (98.6°F).

Storage of Diluted KIRSTY

KIRSTY diluted with Insulin Diluting Medium for KIRSTY to a concentration equivalent to U-10 or equivalent to U-50 prepared as indicated under Dosage and Administration (2.2) may remain in patient use at temperatures up to 30°C (86°F) for 28 days. Discard any unused diluent after opening the vial of Insulin Diluting Medium for KIRSTY.

Storage of KIRSTY in Intravenous Infusion Fluids

Infusion bags prepared as indicated under Dosage and Administration (2.2) are stable at room temperature for 12 hours. Some insulin will be initially adsorbed to the material of the infusion.

17 PATIENT COUNSELING INFORMATION

Advise the patient to read the FDA-approved patient labeling (Patient Information and Instructions for Use).

Never Share a KIRSTY Prefilled Pen Device Between Patients

Advise patients that they must never share a KIRSTY prefilled pen with another person even if the needle is changed, because doing so carries a risk for transmission of blood-borne pathogens. Advise patients using KIRSTY vials not to share needles or syringes with another person. Sharing poses a risk for transmission of blood-borne pathogens [see Warnings and Precautions (5.1)].

Hyperglycemia or Hypoglycemia

Inform patients that hypoglycemia is the most common adverse reaction with insulin. Instruct patients on self-management procedures including glucose monitoring, proper injection technique, and management of hypoglycemia and hyperglycemia, especially at initiation of KIRSTY therapy. Instruct patients on handling of special situations such as intercurrent conditions (illness, stress, or emotional disturbances), an inadequate or skipped insulin dose, inadvertent administration of an increased insulin dose, inadequate food intake, and skipped meals. Instruct patients on the management of hypoglycemia [see Warnings and Precautions (5.3)].

Inform patients that their ability to concentrate and react may be impaired as a result of hypoglycemia. Advise patients who have frequent hypoglycemia or reduced or absent warning signs of hypoglycemia to use caution when driving or operating machinery.

Advise patients that changes in insulin regimen can predispose to hyperglycemia or hypoglycemia and that changes in insulin regimen should be made under close medical supervision [see Warnings and Precautions (5.2)].

Hypoglycemia with Medication Errors

Instruct patients to always check the insulin label before each injection to avoid mix-ups between insulin products [see Warnings and Precautions (5.3)].

Hypersensitivity Reactions

Advise patients that hypersensitivity reactions have occurred with insulin aspart products. Inform patients of the symptoms of hypersensitivity reactions [see Warnings and Precautions (5.4)].

Patients Using Continuous Subcutaneous Insulin Pumps

- Train patients in both intensive insulin therapy with multiple injections and in the function of their pump and pump accessories.
- This KIRSTY product can be used with continuous subcutaneous insulin infusion pumps labeled for use with KIRSTY or NOVOLOG -refer to the insulin pump user manual to see if KIRSTY or NOVOLOG can be used with the insulin pump, in which case KIRSTY can be used with the pump. See recommended infusion sets in the insulin pump user manual.
- Instruct patients to replace insulin in the reservoir at least every 7 days or according to the user manual, whichever is shorter; infusion sets and infusion set insertion sites should be changed according to the manufacturer’s user manual. By following this schedule, patients avoid insulin degradation, infusion set occlusion, and loss of the insulin preservative.
- Instruct patients to discard insulin exposed to temperatures higher than 37°C (98.6°F).
- Instruct patients to inform physician and select a new site for infusion if infusion site becomes erythematous, pruritic, or thickened.
- Instruct patients of the risk of rapid hyperglycemia and ketosis due to pump malfunction, infusion set occlusion, leakage, disconnection or kinking, and degraded insulin. If these problems cannot be promptly corrected, instruct patients to resume therapy with subcutaneous insulin injection and contact their physician [see Warnings and Precautions (5) and How Supplied/Storage and Handling (16.2)].
- Instruct patients of the risk of hypoglycemia from pump malfunction. If these problems cannot be promptly corrected, instruct patients to resume therapy with subcutaneous insulin injection and contact their physician [see Warnings and Precautions (5) and How Supplied/Storage and Handling (16.2)].

Kirsty™ is a trademark of Biosimilars New Co Ltd; a Biocon Biologics Company. Copyright © 2023 Biocon Biologics Inc. All rights reserved.

Manufactured by:

Biocon Biologics Inc.

245 Main st, 2nd Floor

Cambridge, MA 02142, U.S.A.

U.S License No. 2324

Product of Malaysia

PATIENT INFORMATION

KIRSTY™ (kir-Stee)
(insulin aspart-xjhz)

injection, for subcutaneous or intravenous use

Do not share your KIRSTY prefilled pen with other people, even if the needle has been changed. You may give other people a serious infection, or get a serious infection from them.

What is KIRSTY?

KIRSTY is a man-made insulin that is used to control high blood sugar in adults and children with diabetes mellitus.

Who should not take KIRSTY? Do not take KIRSTY if you:

- are having an episode of low blood sugar (hypoglycemia).
- have an allergy to insulin aspart products or any of the ingredients in KIRSTY.

Before taking KIRSTY, tell your healthcare provider about all your medical conditions, including if you are:

- pregnant, planning to become pregnant, or are breastfeeding.
- taking new prescription or over-the-counter medicines, vitamins, or herbal supplements.

Before you start taking KIRSTY, talk to your healthcare provider about low blood sugar and how to manage it.

How should I take KIRSTY?

- Read the Instructions for Use that come with your KIRSTY.
- Take KIRSTY exactly as your healthcare provider tells you to.
- KIRSTY starts acting fast. You should eat a meal within 5 to 10 minutes after you take your dose of KIRSTY.
- Know the type and strength of insulin you take. Do not change the type of insulin you take unless your healthcare provider tells you to. The amount of insulin and the best time for you to take your insulin may need to change if you take different types of insulin.
- Check your blood sugar levels. Ask your healthcare provider what your blood sugars should be and when you should check your blood sugar levels.
- Do not reuse or share your needles with other people. You may give other people a serious infection or get a serious infection from them.
- KIRSTY can be injected under the skin (subcutaneously) of your stomach area (abdomen), buttocks, upper legs (thighs), or upper arms or by continuous infusion under the skin (subcutaneously) through an insulin pump into an area of your body recommended in the instructions that come with your insulin pump.
- Change (rotate) your injection sites within the area you choose with each dose to reduce your risk of getting lipodystrophy (pits in skin or thickened skin) and localized cutaneous amyloidosis (skin with lumps) at the injection sites.
  - Do not use the exact same spot for each injection.
  - Do not inject where the skin has pits, is thickened, or has lumps.
  - Do not inject where the skin is tender, bruised, scaly or hard, or into scars or damaged skin.

What should I avoid while taking KIRSTY? While taking KIRSTY do not:

- Drive or operate heavy machinery, until you know how KIRSTY affects you.
- Drink alcohol or use prescription or over-the-counter medicines that contain alcohol.

What are the possible side effects of KIRSTY?

KIRSTY may cause serious side effects that can lead to death, including:

Low blood sugar (hypoglycemia). Signs and symptoms that may indicate low blood sugar include:

- dizziness or light-headedness
- sweating
- confusion
- headache

- blurred vision
- slurred speech
- shakiness
- fast heartbeat

- anxiety, irritability or mood changes
- hunger

Your insulin dose may need to change because of:

- change in level of physical activity or exercise
- weight gain or loss

- increased stress
- illness

- change in diet

Other common side effects of KIRSTY may include:

- low potassium in your blood (hypokalemia), reactions at the injection site, itching, rash, serious allergic reactions (whole body reactions), skin thickening or pits at the injection site (lipodystrophy), weight gain, and swelling of your hands and feet.

Get emergency medical help if you have:

- trouble breathing, shortness of breath, fast heartbeat, swelling of your face, tongue, or throat, sweating, extreme drowsiness, dizziness, confusion.

These are not all the possible side effects of KIRSTY. Call your doctor for medical advice about side effects. You may report side effects to FDA at 1-800-FDA-1088.

General information about the safe and effective use of KIRSTY.

Medicines are sometimes prescribed for purposes other than those listed in a Patient Information leaflet. Do not use KIRSTY for a condition for which it was not prescribed. Do not give KIRSTY to other people, even if they have the same symptoms that you have. It may harm them.

You can ask your pharmacist or healthcare provider for information about KIRSTY that is written for health professionals.

What are the ingredients in KIRSTY?

Active ingredient: insulin aspart-xjhz

Inactive Ingredients: dibasic sodium phosphate , glycerin, m-cresol, phenol, sodium chloride, zinc, and Water for Injection, USP. Hydrochloric acid 1% and/or sodium hydroxide 1% may be added to adjust pH.

Manufactured by: Biocon Biologics Inc. 245 Main st, 2nd Floor, Cambridge, MA 02142, U.S.A.

U.S License No. 2324, Product of Malaysia

This Patient Information has been approved by the U.S. Food and Drug Administration. Approved: 07/2025

INSTRUCTIONS FOR USE

KIRSTY™ (kir-Stee)
(insulin aspart-xjhz)

injection, for subcutaneous use
10 mL multiple-dose vial: 100 units/mL (U-100)

Read this Instructions for Use before you start taking KIRSTY and each time you get a refill.

There may be new information. This information does not take the place of talking to your healthcare provider about your medical condition or your treatment.

Supplies you will need to give your KIRSTY injection:

- 10 mL KIRSTY vial
- insulin syringe and needle
- alcohol swabs

Preparing your KIRSTY dose:

- Wash your hands with soap and water.
- Before you start to prepare your injection, check the KIRSTY label to make sure that you are taking the right type of insulin. This is especially important if you use more than 1 type of insulin.
- KIRSTY should look clear and colorless. Do not use KIRSTY if it is thick, cloudy, or is colored.
- Do not use KIRSTY past the expiration date printed on the label.

Step 1: Pull off the tamper resistant cap (See Figure A).

Step 2: Wipe the rubber stopper with an alcohol swab (See Figure B).

Step 3: Hold the syringe with the needle pointing up. Pull down on the plunger until the black tip reaches the line for the number of units for your prescribed dose (See Figure C).

Step 4: Push the needle through the rubber stopper of the KIRSTY vial (See Figure D).

Step 5: Push the plunger all the way in. This puts air into the KIRSTY vial (See Figure E).

Step 6: Turn the KIRSTY vial and syringe upside down and slowly pull the plunger down until the black tip is a few units past the line for your dose (See Figure F).

- If there are air bubbles, tap the syringe gently a few times to let any air bubbles rise to the top (See Figure G).

Step 7: Slowly push the plunger up until the black tip reaches the line for your KIRSTY dose (See Figure H).

Step 8: Check the syringe to make sure you have the right dose of KIRSTY.

Step 9: Pull the syringe out of the vial’s rubber stopper (See Figure I).

Giving your injection:

- Inject your KIRSTY exactly as your healthcare provider has shown you. Your healthcare provider should tell you if you need to pinch the skin before injecting.
- KIRSTY can be injected under the skin (subcutaneously) of your stomach area, buttocks, upper legs or upper arms, infused in an insulin pump (continuous subcutaneous infusion into an area of your body recommended in the instructions that come with your insulin pump), or given through a needle in your arm (intravenously) by your healthcare provider.
- If you inject KIRSTY, change (rotate) your injection sites within the area you choose for each dose to reduce your risk of getting lipodystrophy (pits in skin or thickened skin) and localized cutaneous amyloidosis (skin with lumps) at the injection sites. Do not use the same injection site for each injection. Do not inject where the skin has pits, is thickened, or has lumps. Do not inject where the skin is tender, bruised, scaly or hard, or into scars or damaged skin.
- If you use KIRSTY in an insulin pump, you should change your infusion set and insertion site according to the manufacturer’s user manual. KIRSTY can be used with the continuous subcutaneous insulin infusion pumps labeled for use with KIRSTY or NOVOLOG. Read the insulin pump user manual to see if KIRSTY or NOVOLOG can be used. KIRSTY should be given into an area of your body recommended in the instructions that come with your insulin pump. Change (rotate) your insertion sites within the area you choose for each insertion to reduce your risk of getting lipodystrophy (pits in skin or thickened skin) and localized cutaneous amyloidosis (skin with lumps) at the insertion sites. Do not insert into the exact same spot for each insertion. Do not insert where the skin has pits, is thickened, or has lumps. Do not insert where the skin is tender, bruised, scaly or hard, or into scars or damaged skin. The insulin in the reservoir should be changed at least every 7 days or according to the pump user manual, whichever is shorter, even if you have not used all of the insulin.
- If you use KIRSTY in an insulin pump, see your insulin pump manual for instructions or talk to your healthcare provider.
- NPH insulin is the only type of insulin that can be mixed with KIRSTY. Do not mix KIRSTY with any other type of insulin.
- KIRSTY should only be mixed with NPH insulin if it is going to be injected right away under your skin (subcutaneously).
- KIRSTY should be drawn up into the syringe before you draw up your NPH insulin.
- Talk to your healthcare provider if you are not sure about the right way to mix KIRSTY and NPH insulin.

Step 10: Choose your injection site (stomach area, buttocks, upper legs or upper arms) and wipe the skin with an alcohol swab. Let the injection site dry before you inject your dose (See Figure J).

Step 11: Insert the needle into your skin. Push down on the plunger to inject your dose (See Figure K). The needle should remain in the skin for at least 6 seconds to make sure you have injected all the insulin.

Step 12: Pull the needle out of your skin. After that, you may see a drop of KIRSTY at the needle tip. This is normal and does not affect the dose you just received (See Figure L).

- If you see blood after you take the needle out of your skin, press the injection site lightly with a piece of gauze or an alcohol swab. Do not rub the area.

After your injection:

- Do not recap the needle. Recapping the needle can lead to a needle stick injury.
- Put the empty insulin vials, used needles and syringes in a FDA-cleared sharps disposal container right away after use. Do not throw away (dispose of) loose needles and syringes in your household trash.
- If you do not have a FDA-cleared sharps disposal container, you may use a household container that is:
  - made of a heavy-duty plastic,
  - can be closed with a tight-fitting, puncture-resistant lid, without sharps being able to come out,
  - upright and stable during use,
  - leak-resistant, and properly labeled to warn of hazardous waste inside the container.
- When your sharps disposal container is almost full, you will need to follow your community guidelines for the right way to dispose of your sharps disposal container. There may be state or local laws about how you should throw away used needles and syringes. For more information about safe sharps disposal, and for specific information about sharps disposal in the state that you live in, go to the FDA’s website at: http://www.fda.gov/safesharpsdisposal.
- Do not dispose of your used sharps disposal container in your household trash unless your community guidelines permit this. Do not recycle your used sharps disposal container.

How should I store KIRSTY?

- Do not freeze KIRSTY. Do not use KIRSTY if it has been frozen.
- Keep KIRSTY away from heat or light.
- All unopened vials:
  - Store unopened KIRSTY vials in the refrigerator at 36°F to 46°F (2°C to 8°C).
  - Unopened vials may be used until the expiration date printed on the label, if they have been stored in the refrigerator.
  - Unopened vials should be thrown away after 28 days, if they are stored at room temperature up to 86°F (30°C).

- After vials have been opened:
  - Opened KIRSTY vials can be stored in the refrigerator at 36°F to 46°F (2°C to 8°C) or at room temperature up to 86°F (30°C).
  - Throw away all opened KIRSTY vials after 28 days, even if they still have insulin left in them.
  - If using KIRSTY in a pump, throw away all opened KIRSTY vials after 19 days.

General information about the safe and effective use of KIRSTY

- Always use a new syringe and needle for each injection.
- Do not share syringes or needles.
- Keep KIRSTY vials, syringes, and needles out of the reach of children.

This Instructions for Use has been approved by the U.S. Food and Drug Administration.

KIRSTY™ is a trademark of Biosimilars New Co Ltd; a Biocon Biologics Company.

Copyright © 2023 Biocon Biologics Inc. All rights reserved.

Manufactured by:
Biocon Biologics Inc.
245 Main st, 2nd Floor
Cambridge, MA 02142, U.S.A.
U.S. License No. 2324

Product of Malaysia

Approved: 07/2025

INSTRUCTIONS FOR USE

KIRSTY (kir-Stee)
(insulin aspart-xjhz) injection, for subcutaneous use
Prefilled Pen

Introduction

Please read the following instructions carefully before using your KIRSTY Prefilled Pen.

Do not share your KIRSTY Prefilled Pen with other people, even if the needle has been changed. You may give other people a serious infection, or get a serious infection from them.

KIRSTY Prefilled Pen is a disposable, single-patient-use, dial-a-dose insulin pen.

You can select doses from 1 to 80 units in increments of 1 unit.

Only use needles that are compatible for use with KIRSTY Prefilled Pen which are sold separately, including needles from Embecta (such as Embecta UltraFine),

People who are blind or have vision problems should not use this Pen without help from a person trained to use the Pen.

Getting ready

Make sure you have the following items:

- KIRSTY Prefilled Pen
- a new sterile needle (see Step B)
- Alcohol swabs

KIRSTY Prefilled Pen

Needle (example)

Preparing your KIRSTY Prefilled Pen

- Wash your hands with soap and water.
- Before you start to prepare your injection, check the label to make sure that you are taking the right type of insulin. This is especially important if you take more than 1 type of insulin.
- KIRSTY should look clear and colorless. Do not use your KIRSTY Prefilled Pen if the liquid contains particles or is colored.

A. Pull off the pen cap (see diagram A).
  Wipe the rubber stopper with an alcohol swab.

B. Attaching the needle
  Remove the protective tab from a disposable needle.
  Screw the needle tightly onto your Prefilled Pen. It is important that the needle is put on straight (see diagram B).
  Never place a disposable needle on your KIRSTY Prefilled Pen until you are ready to take your injection.

C. Pull off the big outer needle cap (see diagram C).

D. Pull off the inner needle cap and throw it away (dispose of it) (see diagram D).

! Always use a new needle for each injection to make sure the needle is free of germs (sterile) and to prevent blocked needles. Do not reuse or share your needles with other people. You may give other people a serious infection, or get a serious infection from them.
! Be careful not to bend or damage the needle before use.
! To reduce the risk of unexpected needle sticks, never put the inner needle cap back on the needle.

Giving the airshot before each injection

Before each injection small amounts of air may collect in the cartridge during normal use. To avoid injecting air and to ensure proper dosing:

E. Turn the dose selector to select 2 units (see diagram E).

F. Hold your KIRSTY Prefilled Pen with the needle pointing up.
  Tap the cartridge gently with your finger a few times to make any air bubbles collect at the top of the cartridge (see diagram F).

G. Keep the needle pointing upwards, press the push-button all the way in (see diagram G). The dose selector returns to 0.
  A drop of insulin should appear at the needle tip. If not, change the needle and repeat the procedure no more than 6 times.
  If you do not see a drop of insulin after 6 times, do not use the KIRSTY Prefilled Pen and contact Biocon Biologics Inc. at 1-833-986-1468.
  A small air bubble may remain at the needle tip, but it will not be injected.

Selecting your dose

Check and make sure that the dose selector is set at 0.

H. Turn the dose selector to the number of units you need to inject.
  The pointer should line up with your dose.
  The dose can be corrected either up or down by turning the dose selector in either direction until the correct dose lines up with the pointer (see diagram H). When turning the dose selector, be careful not to press the push-button as insulin will come out.
  You cannot select a dose larger than the number of units left in the cartridge.
  You will hear a click for every single unit dialed. Do not set the dose by counting the number of clicks you hear because you may get an incorrect dose.
! Do not use the cartridge scale printed on the cartridge to measure your dose of insulin.

Giving the injection

Do the injection exactly as shown to you by your healthcare provider. Your healthcare provider should tell you if you need to pinch the skin before injecting. Wipe the skin with an alcohol swab and let the area dry.

KIRSTY can be injected under the skin (subcutaneously) of your stomach area, buttocks, upper legs (thighs), or upper arms.

Change (rotate) your injection sites within the area you choose for each dose to reduce your risk of getting lipodystrophy (pits in skin or thickened skin) and localized cutaneous amyloidosis (skin with lumps) at the injection sites. Do not use the same injection site for each injection. Do not inject where the skin has pits, is thickened, or has lumps. Do not inject where the skin is tender, bruised, scaly or hard, or into scars or damaged skin.

I. Insert the needle into your skin.
  Inject the dose by pressing the push-button all the way in until the 0 lines up with the pointer (see diagram I). Be careful only to push the button when injecting.
  Turning the dose selector will not inject insulin.

J. Keep the needle in the skin for at least 6 seconds, and keep the push-button pressed all the way in until the needle has been pulled out from the skin (see diagram J). This will make sure that the full dose has been given.
  You may see a drop of insulin at the needle tip. This is normal and has no effect on the dose you just received. If blood appears after you take the needle out of your skin, press the injection site lightly with an alcohol swab.
! Do not rub the area.

After the injection

Do not recap the needle. Recapping can lead to a needle stick injury. Remove the needle from the KIRSTY Prefilled Pen after each injection and dispose of it. This helps to prevent infection, leakage of insulin, and will help to make sure you inject the right dose of insulin.

If you do not have a sharps container, carefully slip the needle into the outer needle cap. Safely remove the needle and throw it away as soon as you can.

- Put your used needles in an FDA-cleared sharps disposal container right away after use. Do not throw away (dispose of) loose needles in your household trash.
- If you do not have an FDA-cleared sharps disposal container, you may use a household container that is:
  - made of a heavy-duty plastic,
  - can be closed with a tight-fitting, puncture-resistant lid, without sharps being able to come out,
  - upright and stable during use,
  - leak-resistant, and
  - properly labeled to warn of hazardous waste inside the container
- When your sharps disposal container is almost full, you will need to follow your community guidelines for the right way to dispose of your sharps disposal container. There may be state or local laws about how you should throw away used needles and syringes. For more information about safe sharps disposal, and for specific information about sharps disposal in the state that you live in, go to the FDA’s website at: http://www.fda.gov/safesharpsdisposal.
- Do not dispose of your used sharps disposal container in your household trash unless your community guidelines permit this. Do not recycle your used sharps disposal container.
- When there is not enough medicine left in your KIRSTY Prefilled Pen for your prescribed dose, the KIRSTY Prefilled Pen may be thrown away in your household trash after you have removed the needle.

The KIRSTY Prefilled Pen prevents the cartridge from being completely emptied. It is designed to deliver 300 units.

K. Put the pen cap on the KIRSTY Prefilled Pen and store the KIRSTY Prefilled Pen without the needle attached (see diagram K). Storing without the needle attached helps prevent leaking, blocking of the needle, and air from entering the Pen.

How should I store KIRSTY Prefilled Pen?

- Do not freeze KIRSTY. Do not use KIRSTY if it has been frozen.
- Keep KIRSTY away from heat or light.
- Store the KIRSTY Prefilled Pen without the needle attached.

Until first use:

- Store unused KIRSTY Prefilled Pen in the refrigerator at 36°F to 46°F (2°C to 8°C).
- Unused KIRSTY Prefilled Pen may be used until the expiration date printed on the label, if kept in the refrigerator.
- Unused KIRSTY Prefilled Pen stored at room temperature up to 86°F (30°C) should be thrown away after 28 days.

In-use:

- Store the KIRSTY Prefilled Pen you are currently using out of the refrigerator at room temperature up to 86°F (30°C) for up to 28 days.
- The KIRSTY Prefilled Pen you are using should be thrown away after 28 days, even if it still has insulin left in it.

Maintenance

For the safe and proper use of your Prefilled Pen be sure to handle it with care. Avoid dropping your Prefilled Pen as it may damage it. If you are concerned that your Prefilled Pen is damaged, use a new one. You can clean the outside of your Prefilled Pen by wiping it with a damp cloth. Do not soak or wash your Prefilled Pen as it may damage it. Do not refill your Prefilled Pen.

! Remove the needle from the KIRSTY Prefilled Pen after each injection. This helps to ensure sterility, prevent leakage of insulin, and will help to make sure you inject the right dose of insulin for future injections.
! Be careful when handling used needles to avoid needle sticks and transfer of infectious diseases.
! Keep your KIRSTY Prefilled Pen and needles out of the reach of children.
! Use KIRSTY Prefilled Pen as directed to treat your diabetes.
! Do not share your KIRSTY Prefilled Pen or needles with other people.
! You may give other people a serious infection, or get a serious infection from them.
! Always use a new needle for each injection.
! Biocon Biologics Inc. is not responsible for harm due to using this insulin pen with products not recommended by Biocon Biologics Inc.
! As a precautionary measure, always carry a spare insulin delivery device in case your KIRSTY Prefilled Pen is lost or damaged.
! Remember to keep the disposable KIRSTY Prefilled Pen with you. Do not leave it in a car or other location where it can get too hot or too cold.

BD is a registered trademark of Becton, Dickinson and Company.

This Instructions for Use has been approved by the U.S. Food and Drug Administration.

KIRSTY™ is a trademark of Biosimilars New Co. Ltd.; a Biocon Biologics Company.

Copyright © 2023 Biocon Biologics Inc. All rights reserved.

Manufactured by:
Biocon Biologics Inc.
245 Main st, 2nd Floor
Cambridge, MA 02142, U.S.A.
U.S. License No. 2324

Product of Malaysia

Approved: 07/2025

PRINCIPAL DISPLAY PANEL 10mL

NDC 83257-007-11

Kirsty™
(insulin aspart-xjhz)
injection
100 units/mL (U-100)

For intravenous or subcutaneous use
Use only with a U-100 syringe.

Rx only

One 10 mL
Multiple-Dose Vial.

Store refrigerated at 2°C to 8°C (36°F to 46°F) until first use then store either refrigerated or at room temperature (up to 30°C [86°F]) and discard after 28 days. Avoid freezing. Protect from light.

Warning: Any change of insulin should be made cautiously and only under medical supervision (see package insert).

Dosage: see Prescribing Information.

Discard unused portion of the vial 28 days after first opening.

Date of first opening: __/__/__.

Each mL contains 100 units of insulin aspart-xjhz, and the inactive ingredients dibasic sodium phosphate (0.997 mg), glycerin (16 mg), m-cresol (1.72 mg), phenol (1.50 mg), sodium chloride (0.58 mg), zinc (19.6 mcg), and Water for Injection, USP. The pH is 7.0 to 7.8. Hydrochloric acid and sodium hydroxide may be added to adjust pH.

Manufactured by:

Biocon Biologics Inc.

245 Main St, 2nd Floor Cambridge, MA 02142, U.S.A.

U.S. License No. 2324

Product of Malaysia

PRINCIPAL DISPLAY PANEL 3mL

NDC 83257-008-32

Kirsty™
(insulin aspart-xjhz) injection
For Single Patient Use Only
100 units/mL (U-100)

For Subcutaneous Use.

Dispense in this sealed carton.

*Needles not included.

Five 3 mL Prefilled Pens

Rx only
Store refrigerated at 36° to 46°F (2° to 8°C) until first use. Avoid freezing. Protect from light. After first use of a Kirsty pen, store the pen at room temperature (up to 30°C [86°F]) for up to 28 days.

Warning

Any changes of insulin should be made cautiously and only under medical supervision.

Kirsty™ Prefilled Pen is for single patient use only.

Dosage: see Prescribing Information.

*Needles not included.

For Subcutaneous Use.

Each mL contains 100 units of insulin aspart-xjhz, and the inactive ingredients dibasic sodium phosphate (0.997 mg), glycerin (16 mg), m-cresol (1.72 mg), phenol (1.50 mg), sodium chloride (0.58 mg), zinc (19.6 mcg), and Water for Injection, USP. The pH is 7.0 to 7.8.

Hydrochloric acid and sodium hydroxide may be added to adjust pH.

Store refrigerated at 2°C to 8°C (36°F to 46°F) until first use. Avoid freezing.

Protect from light. After first use of a Kirsty pen, store the pen at room temperature (up to 30°C [86°F]) for up to 28 days.

Discard unused portion of the pen 28 days after first opening.

Date of first opening:

Pen 1: _____ / _____ / ______.

Pen 2: _____ / _____ / ______.

Pen 3: _____ / _____ / ______.

Pen 4: _____ / _____ / ______.

Pen 5: _____ / _____ / ______.

*Embecta Ultra-fine needles are compatible with Kirsty™. These are sold separately and manufactured by Embecta.

Manufactured by:

Biocon Biologics Inc.

245 Main St, 2nd Floor, Cambridge, MA 02142, U.S.A.

U.S. License No. 2324 Product of Malaysia

PRINCIPAL DISPLAY PANEL 10mL - Diluting Medium

NDC 83257-006-11

Insulin Diluting Medium for Kirsty™
Use only with Kirsty
This product does not contain insulin.

10 mL

Single-dose vial

Discard unused portion.

Each mL of Diluting Medium contains dibasic sodium phosphate (0.997 mg), glycerin (16 mg), m-cresol (1.5 mg), phenol (0.65 mg), and Water for Injection. Hydrochloric acid and sodium hydroxide may be added to adjust pH.

CAUTION: For use by health professionals only to dilute Kirsty or Insulin Aspart (insulin apsart-xjhz) Injection products.

Dilutions should be performed under aseptic conditions. Store unused vials at 2°C to 8°C (36°F to 46°F) and protect from light and heat – do not freeze.

Do not use the diluting medium if it does not appear water-clear and colorless or if the cap is loose or missing. The diluted insulin preparation should not be mixed with other insulin preparations in the same syringe. Do not use the diluting medium in insulin pumps. Never use diluting medium after the expiration date printed on the box or vial label.

Keep out of reach of children.

Manufactured by:

Biocon Biologics Inc.

245 Main St, 2nd Floor Cambridge, MA 02142, U.S.A.

U.S. License No. 2324 Product of Malaysia